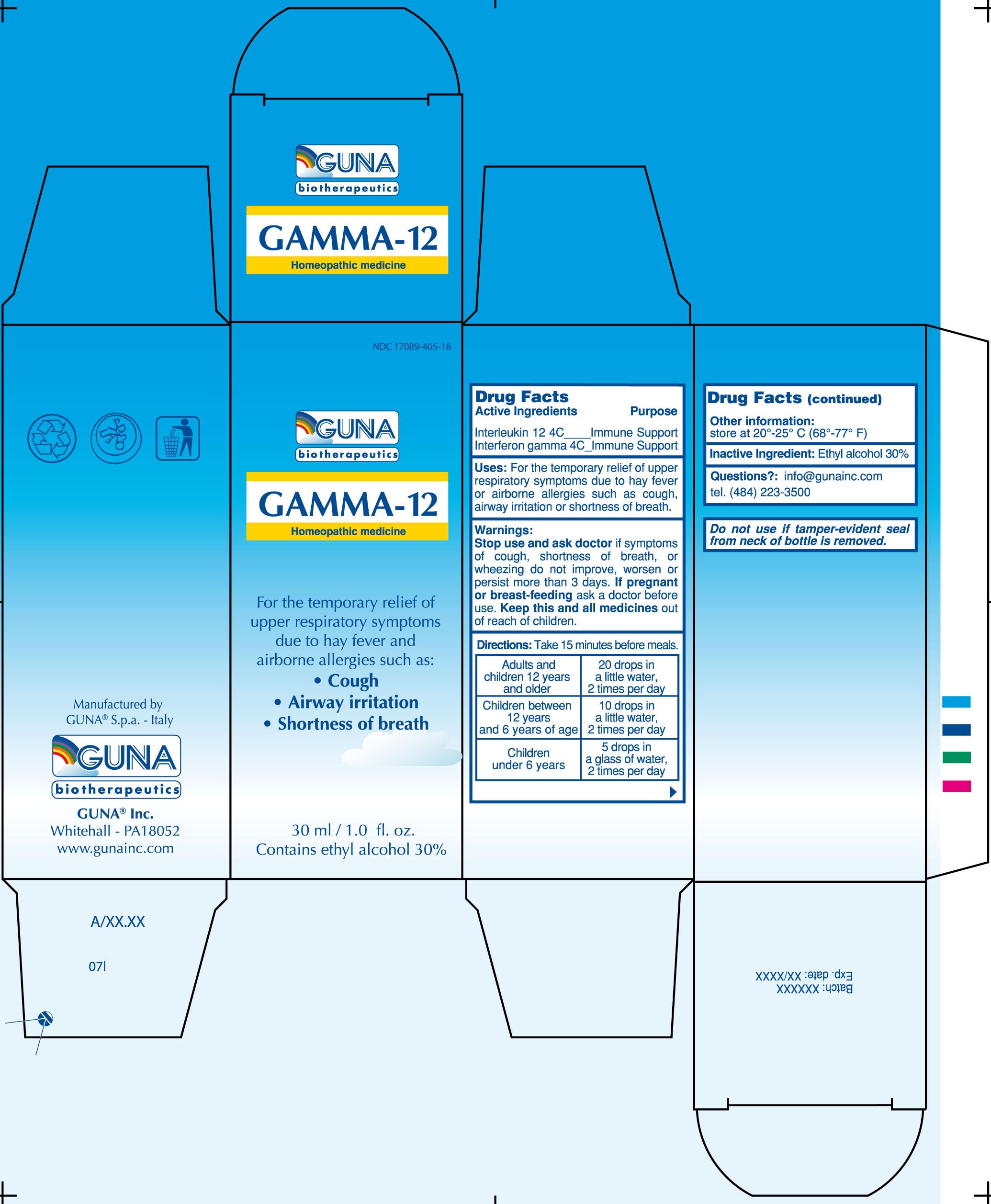 DRUG LABEL: GAMMA -12
NDC: 17089-405 | Form: SOLUTION/ DROPS
Manufacturer: Guna spa
Category: homeopathic | Type: HUMAN OTC DRUG LABEL
Date: 20221115

ACTIVE INGREDIENTS: INTERFERON GAMMA-1B 4 [hp_C]/30 mL; INTERLEUKIN-12 HUMAN RECOMBINANT 4 [hp_C]/30 mL
INACTIVE INGREDIENTS: ALCOHOL 9 mL/30 mL

GAMMA 12

ACTIVE INGREDIENTS/PURPOSE

INTERFERON GAMMA 4C IMMUNE SUPPORT
INTERLEUKIN-12 4C IMMUNE SUPPORT

USES

For the temporary relief of upper respiratory symptoms due to hay fever or airborne allergies such as: -Cough –Airway irritation –Shortness of breath

WARNINGS

Stop use and ask doctor if symptoms of cough, shortness of breath, or wheezing do not improve, worsen or persist more than 3 days

PREGNANCY

If pregnant or breast-feeding ask a doctor before use

WARNINGS

Keep this and all medicines out of reach of children

DIRECTIONS

Take 15 minutes before meals

Adults and children 12 years and older

20 drops in a little water, 2 times per day

Children between 12 years and 6 years of age

10 drops in a little water, 2 times per day

Children under 6 years

5 drops in a glass of water, 2 times per day

QUESTIONS

Questions?: info@gunainc.com
tel. (484) 223-3500

inactive ingredient: Ethyl alcohol 30%.

INDICATIONS AND USAGE

take 15 minutes before meals